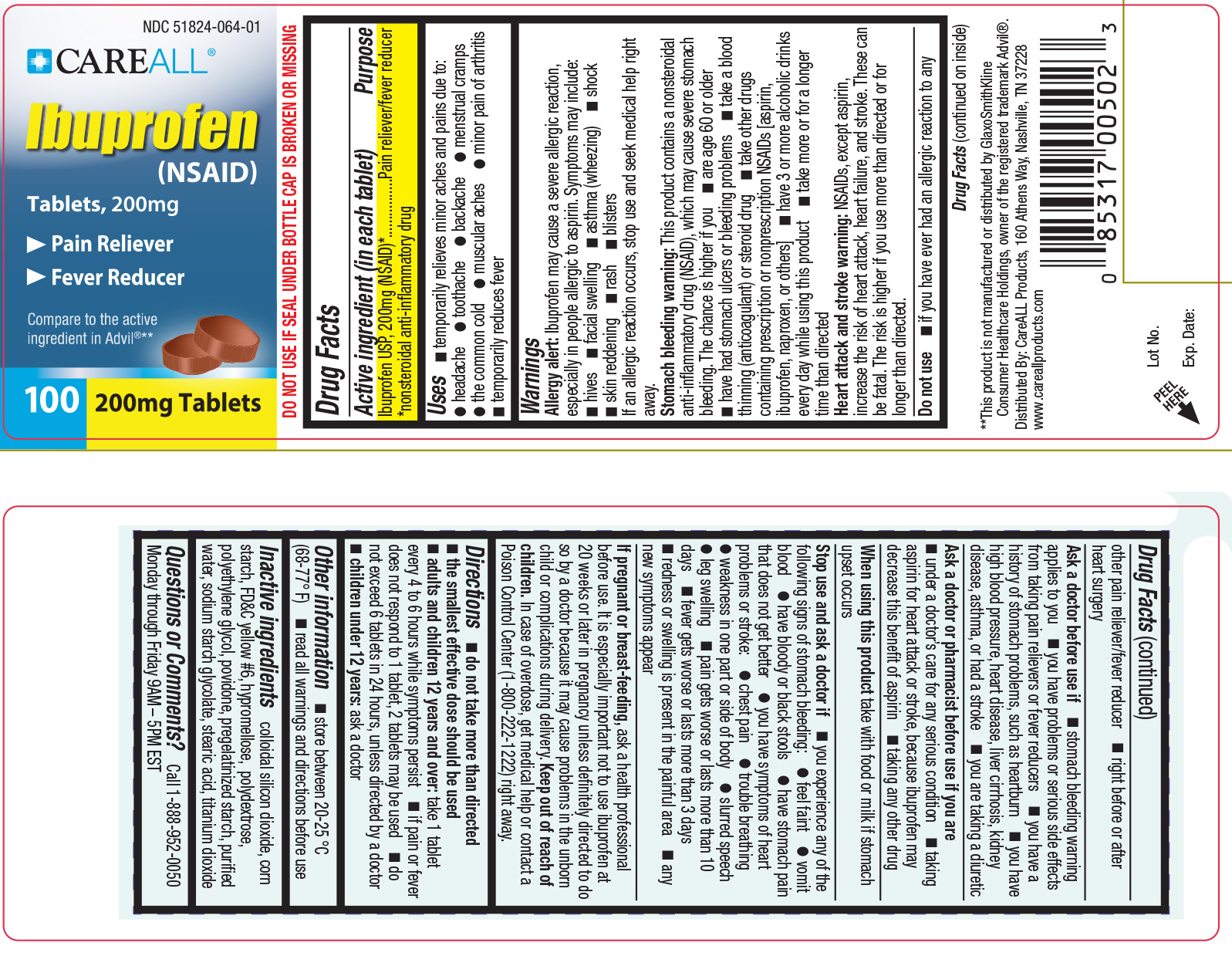 DRUG LABEL: CAREALL Ibuprofen
NDC: 51824-064 | Form: TABLET
Manufacturer: New World Imports
Category: otc | Type: HUMAN OTC DRUG LABEL
Date: 20251201

ACTIVE INGREDIENTS: IBUPROFEN 200 mg/1 1
INACTIVE INGREDIENTS: STARCH, CORN; HYPROMELLOSES; SILICON DIOXIDE; FD&C YELLOW NO. 6; POVIDONE; WATER; STEARIC ACID; TITANIUM DIOXIDE; POLYDEXTROSE; POLYETHYLENE GLYCOL, UNSPECIFIED; SODIUM STARCH GLYCOLATE TYPE A POTATO

Drug Facts

ACTIVE INGREDIENT

Ibuprofen 200mg (NSAID)**

**nonsteroidal anti-inflammatory drug

PURPOSE

Pain reliever / fever reducer

KEEP OUT OF REACH OF CHILDREN

In case of overdose, get medical help or contact a Poison Control Center right away (1-800-222-1222)

INDICATIONS AND USAGE

Temporarily relieves minor aches and pains due to:

Headache, toothache, backache, menstrual cramps, the common cold, muscular aches, minor pain of arthritis.

Temporarily reduces fever

Allergy alert:Ibuprofen may cause a severe allergic reaction, especially in people allergic to aspirin. Symptoms may include:

hives, facial swelling, asthma (wheezing), shock, skin reddening, rash, blisters

If an allergic reaction occurs, stop use and seek medical help right away.

Stomach bleeding warning:This product contains a nonsteroidal anti-inflammatory drug (NSAID), which may cause severe stomach bleeding. The chance is higher if you are 60 years or older, have had stomach ulcers or bleeding problems, take a blood thinning (anticoaglant) or steroid drug, take other drugs containing a NSAID [aspirin, ibuprofen, naproxen, or others], have 3 or more alcoholic drinks every day while using this product, or take more / for a longer time than directed.

Heart attack and stroke warning:NSAID's, except aspirin, increase the risk of heart attack, heart failure, and stroke. These can be fatal. The risk is higher if you use more than directed or for longer than directed.

Do not useif you have ever had an allergic reaction to any other pain reliever / fever reducer or right before or after heart surgery.

Ask a doctor before use if:stomach bleeding warning applies to you. you have problems or serious side effects from taking pain relievers or fever reducers. You have a history of stomach problems, such as heartburn. You have high blood pressure, heart disease, liver cirrhosis, kidney disease, asthma, or had a stroke. You are taking a diuretic.

Ask a doctor or pharmacist before use if you are:taking aspirin for heart attack or stroke, because ibuprofen may decrease this benefit of aspirin. Under a doctor's care for any serious condition. Taking any other drug.

When using this product:take with food or milk if stomach upset occurs.

Stop use and ask a doctor if:You experience any of the following signs of stomach bleeding: feel faint, vomit blood, have bloody or black stools, have stomach pain that does not get better You have symptoms of heart problems or stroke: chest pain, trouble breathing, weakness in one part or side of body, slurred speech, or leg swelling. Pain gets worse or lasts more than 10 days. Fever gets worse or lasts more than 3 days. Redness or swelling is present in the painful area. Any new symptoms appear.

Pregnant or breast-feeding:ask a health professional before use. It is especially important not to use ibuprofen during the last 3 months of pregnancy unless definitely directed to do so by a doctor because it may cause problems in the unborn child or complications during delivery.

DOSAGE AND ADMINISTRATION

Do not take more than directed. The smallest effective dose should be used.

Adult and children 12 years and older:Take 1 tablets every 4 to 6 hours while symptoms persist. If pain or fever does not respond to 1 tablets, 2 tablets may be used. Do not exceed 6 tablets in 24 hours unless directed by a doctor.

Children under 12 years:ask a doctor

INACTIVE INGREDIENT

colloidal silicon dioxide, corn starch, FD and C yellow 6, hypromellose, polydextrose, polyethylene glycol, povidone, pregelatinized starch, purified water, sodium starch glycolate, stearic acid, titanium dioxide

OTHER SAFETY INFORMATION

Store between 20-25 degrees celsius (68-77 degrees farhenheit).

Read all warnings and directions before use

Do not use if seal under bottle cap is broken or missing

Questions or Comments:Call 1-888-952-0050 Monday through Friday 9 AM - 5 PM EST